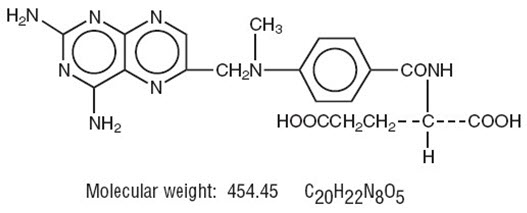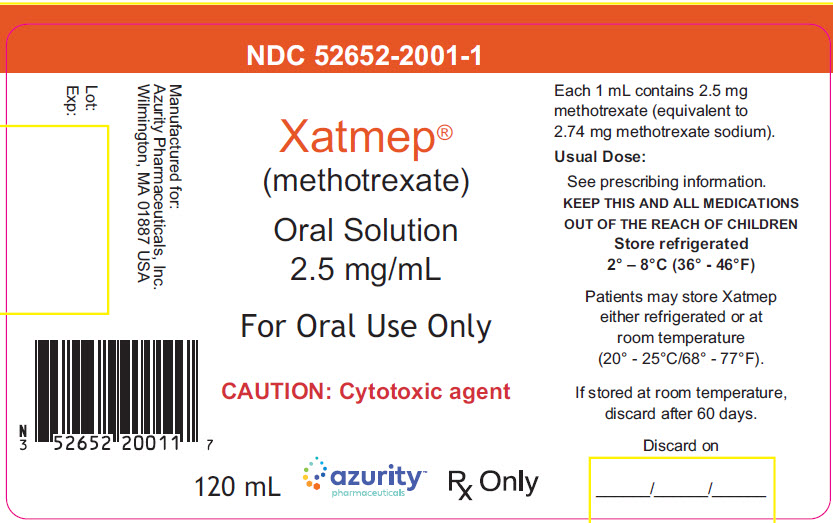 DRUG LABEL: Xatmep
NDC: 52652-2001 | Form: SOLUTION
Manufacturer: Azurity Pharmaceuticals, Inc.
Category: prescription | Type: HUMAN PRESCRIPTION DRUG LABEL
Date: 20251216

ACTIVE INGREDIENTS: METHOTREXATE 2.5 mg/1 mL
INACTIVE INGREDIENTS: WATER; SODIUM CITRATE, UNSPECIFIED FORM; CITRIC ACID MONOHYDRATE; METHYLPARABEN SODIUM; PROPYLPARABEN SODIUM; SUCRALOSE; SODIUM HYDROXIDE; HYDROCHLORIC ACID

HIGHLIGHTS OF PRESCRIBING INFORMATION

These highlights do not include all the information needed to use XATMEP®safely and effectively. See full prescribing information for XATMEP.
XATMEP (methotrexate) oral solution
Initial U.S. Approval: 1953

WARNING: SEVERE TOXIC REACTIONS, INCLUDING EMBRYO-FETAL TOXICITY

See full prescribing information for complete boxed warning.

- Methotrexate can cause severe or fatal toxicities. Monitor closely and modify dose or discontinue for the following toxicities: bone marrow suppression (5.1), infection (5.2), renal (5.3), gastrointestinal (5.4), hepatic (5.5), pulmonary (5.6), hypersensitivity and dermatologic (5.7).
- Methotrexate can cause embryo-fetal toxicity and fetal death. Use in polyarticular juvenile idiopathic arthritis is contraindicated in pregnancy (4). Consider the benefits and risks of XATMEP and risks to the fetus when prescribing XATMEP to a pregnant patient with a neoplastic disease. Advise patients to use effective contraception during and after treatment with XATMEP (5.9, 8.1, 8.3).

1 INDICATIONS AND USAGE

XATMEP is a folate analog metabolic inhibitor indicated for the:

- Treatment of pediatric patients with acute lymphoblastic leukemia (ALL) as a component of a combination chemotherapy maintenance regimen (1.1).
- Management of pediatric patients with active polyarticular juvenile idiopathic arthritis (pJIA) who are intolerant of or had an inadequate response to first-line therapy (1.2).

2 DOSAGE AND ADMINISTRATION

- Use another formulation of methotrexate for patients requiring dosing via routes of administration other than oral (2.1).
- Measure with an accurate measuring device (2.1).

Recommended Dosage:

- ALL: 20 mg/m^2one time weekly (2.2).
- pJIA: Starting dose of 10 mg/m^2one time weekly (2.3).

3 DOSAGE FORMS AND STRENGTHS

Oral solution: 2.5 mg/mL (3).

4 CONTRAINDICATIONS

- Pregnancy (patients with pJIA) (4).
- Severe hypersensitivity to methotrexate (4).

5 WARNINGS AND PRECAUTIONS

- Secondary malignancies can occur. In case of immunosuppression-associated lymphoma, discontinue methotrexate before starting treatment for lymphoma (5.8).
- Immunizations may be ineffective (5.10).
- Effects on reproduction: May cause impairment of fertility, oligospermia and menstrual dysfunction (5.11, 8.3).

6 ADVERSE REACTIONS

Most common adverse reactions are: ulcerative stomatitis, leukopenia, nausea, abdominal distress, and elevated liver function tests. Other frequently reported adverse reactions are malaise, fatigue, chills and fever, dizziness and decreased resistance to infection (6).

To report SUSPECTED ADVERSE REACTIONS, contact Azurity Pharmaceuticals, Inc., at 1-855-379-0383 or FDA at 1-800-FDA-1088 or www.fda.gov/medwatch.

7 DRUG INTERACTIONS

- Oral Antibiotics: May increase hematologic and gastrointestinal toxicity. Monitor patients accordingly (7.1).
- Nitrous Oxide: May increase the risk of toxicity (7.1).
- NSAIDs, Aspirin, and Steroids: May elevate and prolong serum methotrexate levels and increase gastrointestinal toxicity. Monitor patients accordingly (7.1).

8 USE IN SPECIFIC POPULATIONS

Lactation: Advise women not to breastfeed (8.2).

FULL PRESCRIBING INFORMATION

WARNING: SEVERE TOXIC REACTIONS, INCLUDING EMBRYO-FETAL TOXICITY

Methotrexate can cause the following severe or fatal adverse reactions. Monitor closely and modify dose or discontinue methotrexate as appropriate.

- Bone marrow suppression [see Warnings and Precautions (5.1)]
- Serious infections [see Warnings and Precautions (5.2)]
- Renal toxicity and increased toxicity with renal impairment [see Warnings and Precautions (5.3)]
- Gastrointestinal toxicity [see Warnings and Precautions (5.4)]
- Hepatic toxicity [see Warnings and Precautions (5.5)]
- Pulmonary toxicity [see Warnings and Precautions (5.6)]
- Hypersensitivity and dermatologic reactions [see Warnings and Precautions (5.7)]
- Methotrexate can cause embryo-fetal toxicity, including fetal death. Use in pJIA is contraindicated in pregnancy. Consider the benefits and risks of XATMEP and risks to the fetus when prescribing XATMEP to a pregnant patient with a neoplastic disease. Advise females and males of reproductive potential to use effective contraception during and after treatment with XATMEP [see Contraindications (4), Warnings and Precautions (5.9), Use in Specific Populations (8.1, 8.3)].

1 INDICATIONS AND USAGE

1.1 Acute Lymphoblastic Leukemia

XATMEP is indicated for the treatment of pediatric patients with acute lymphoblastic leukemia (ALL) as part of a multi-phase, combination chemotherapy maintenance regimen.

1.2 Polyarticular Juvenile Idiopathic Arthritis

XATMEP is indicated in the management of pediatric patients with active polyarticular juvenile idiopathic arthritis (pJIA) who have had an insufficient therapeutic response to, or are intolerant of, an adequate trial of first-line therapy including full dose non-steroidal anti-inflammatory agents (NSAIDs).

2 DOSAGE AND ADMINISTRATION

2.1 Important Administration Information

XATMEP is intended for oral use only. Use another formulation of methotrexate for alternative dosing in patients who require dosing via other routes of administration. Instruct patients and caregivers that the recommended dose should be taken weekly, as directed, and that mistaken daily use of the recommended dose has led to fatal toxicity [see Warnings and Precautions (5.15), Overdosage (10)].

It is important that XATMEP be measured with an accurate measuring device [see Warnings and Precautions (5.15), Patient Counseling Information (17)] . A household teaspoon is not an accurate measuring device. A pharmacist can provide an appropriate device and can provide instructions for measuring the correct dose.

2.2 Acute Lymphoblastic Leukemia

The recommended starting dose of XATMEP, in multi-agent combination chemotherapy maintenance regimens, is 20 mg/m^2given one time weekly. After initiating XATMEP, continuation of appropriate dosing requires periodic monitoring of absolute neutrophil count (ANC) and platelet count to assure sufficient drug exposure (that is to maintain ANC at a desirable level) and to adjust for excessive hematological toxicity.

2.3 Polyarticular Juvenile Idiopathic Arthritis

The recommended starting dose of XATMEP is 10 mg/m^2given one time weekly.

Dosages should be tailored to the individual patient and adjusted gradually to achieve an optimal response. Although there is experience with doses up to 30 mg/m^2/week in pediatric patients, doses greater than 20 mg/m^2/week may result in a significant increase in the incidence and severity of serious toxic reactions, especially bone marrow suppression. Doses between 20 and 30 mg/m^2/week (0.65 to 1 mg/kg/week) may have better absorption and fewer gastrointestinal side effects if methotrexate is administered by an alternative route using another formulation.

Therapeutic response usually begins within 3 to 6 weeks and the patient may continue to improve for another 12 weeks or more.

Certain side effects such as mouth sores may be reduced by folate supplementation with methotrexate in pJIA.

2.4 Evaluations Prior to Starting Methotrexate

Assess hematologic, hepatic, and renal function before beginning, as well as periodically during and before reinstituting, therapy with XATMEP [see Warnings and Precautions (5.1, 5.3, 5.5, 5.7, 5.14)]. Exclude pregnancy in females of reproductive potential before starting XATMEP [see Contraindications (4), Warnings and Precautions (5.9), Use in Specific Populations (8.1, 8.3)] .

2.5 Handling Information

XATMEP is a cytotoxic drug. Follow applicable special handling and disposal procedures.^1

3 DOSAGE FORMS AND STRENGTHS

XATMEP is a clear yellow to orange oral solution that contains 2.5 mg of methotrexate per milliliter.

4 CONTRAINDICATIONS

XATMEP is contraindicated in the following:

- Pregnancy in patients with non-malignant diseases. XATMEP can cause embryo-fetal toxicity and fetal death when administered during pregnancy [see Warnings and Precautions (5.9), Use in Specific Populations (8.1)] .
- Patients with severe hypersensitivity to methotrexate [see Warnings and Precautions (5.7), Adverse Reactions (6.1, 6.2)] .

5 WARNINGS AND PRECAUTIONS

5.1 Bone Marrow Suppression

XATMEP suppresses hematopoiesis and can cause severe and life-threatening pancytopenia, anemia, leukopenia, neutropenia, and thrombocytopenia.

Obtain blood counts at baseline and periodically during treatment. Monitor patients for possible clinical complications of bone marrow suppression. Provide supportive care and modify dose or discontinue XATMEP as needed.

5.2 Serious Infections

Patients treated with XATMEP are at increased risk for developing life-threatening or fatal bacterial, fungal, or viral infections including opportunistic infections such as Pneumocystis jirovecipneumonia, invasive fungal infections, hepatitis B reactivation, tuberculosis primary infection or reactivation, and disseminated Herpes zosterand cytomegalovirus infections.

Monitor patients for the signs and symptoms of infection during and after treatment with XATMEP and treat promptly. Consider dose modification or discontinuation of XATMEP in patients who develop serious infections [see Warnings and Precautions (5.1)] .

5.3 Renal Toxicity and Increased Toxicity with Renal Impairment

XATMEP can cause renal damage including acute renal failure. Monitor renal function to decrease the risk of renal injury and mitigate renal toxicity.

Consider administration of glucarpidase in patients with toxic plasma methotrexate concentrations (> 1 micromole per liter) and delayed clearance due to impaired renal function [see glucarpidase Prescribing Information].

5.4 Gastrointestinal Toxicity

XATMEP can cause diarrhea, vomiting, stomatitis, hemorrhagic enteritis, and fatal intestinal perforation. Patients with peptic ulcer disease or ulcerative colitis are at a greater risk of developing severe gastrointestinal adverse reactions.

Interrupt or discontinue XATMEP and institute appropriate supportive care as needed.

Unexpectedly severe and fatal gastrointestinal toxicity can occur with concomitant administration of XATMEP (primarily at high dosage) and nonsteroidal anti-inflammatory drugs (NSAIDs) [see Drug Interactions (7.1)].

5.5 Hepatic Toxicity

XATMEP can cause severe and potentially irreversible hepatotoxicity including fibrosis, cirrhosis, and fatal liver failure. Avoid use of XATMEP in patients with chronic liver disease.

Assess liver function prior to initiating XATMEP and monitor liver function tests during treatment. Interrupt or discontinue XATMEP as appropriate. Transient asymptomatic acute liver enzyme elevations are common and are not predictive of subsequent hepatic disease. Persistent abnormalities in liver function tests may precede appearance of fibrosis or cirrhosis.

Other risk factors for hepatotoxicity include alcoholism, obesity, diabetes, hyperlipidemia, previous significant exposure to liver toxins, history of liver disease, family history of inheritable liver disease, persistent abnormal liver chemistry findings, duration of therapy, and advanced age.

5.6 Pulmonary Toxicity

Methotrexate-induced pulmonary toxicity including acute or chronic interstitial pneumonitis and irreversible or fatal cases can occur at all dose levels. Monitor patients for signs of pulmonary toxicity and interrupt or discontinue XATMEP as appropriate.

5.7 Hypersensitivity and Dermatologic Reactions

Severe, including fatal, dermatologic reactions, such as toxic epidermal necrolysis, Stevens-Johnson syndrome, exfoliative dermatitis, skin necrosis, erythema multiforme, can occur with methotrexate. Discontinue XATMEP if severe dermatologic reactions occur.

Anaphylaxis can occur with methotrexate. If anaphylaxis or any other serious hypersensitivity reaction occurs, immediately discontinue methotrexate and institute appropriate therapy. Methotrexate is contraindicated for use in patients with a history of severe hypersensitivity.

Radiation dermatitis and sunburn may be “recalled” by the use of methotrexate.

5.8 Secondary Malignancies

Secondary malignancies can occur at all dose levels of methotrexate.

There have been instances of lymphoproliferative disease associated with low-dose oral methotrexate which have regressed completely following withdrawal of methotrexate without institution of antineoplastic therapy. Discontinue XATMEP first and institute appropriate treatment if the lymphoma does not regress.

5.9 Embryo-Fetal Toxicity

Based on published reports and methotrexate’s mechanism of action, methotrexate can cause embryo-fetal toxicity and fetal death when administered to a pregnant woman. In pregnant women with non-malignant diseases, methotrexate is contraindicated. Consider the benefits and risks of XATMEP and risks to the fetus when prescribing XATMEP to a pregnant patient with a neoplastic disease. Advise females of reproductive potential to use effective contraception during therapy and for 6 months after the final dose. Advise males of reproductive potential to use effective contraception during and for at least 3 months after the final methotrexate dose [see Contraindications (4), Use in Specific Populations (8.1, 8.3), Clinical Pharmacology (12.1)] .

5.10 Ineffective Immunization and Risks Associated with Live Vaccines

Immunization may be ineffective when given during XATMEP therapy.

Immunization with live virus vaccines is not recommended. There have been reports of disseminated vaccinia infections after smallpox immunization in patients receiving methotrexate therapy.

5.11 Effects on Reproduction

Based on published reports, methotrexate can cause impairment of fertility, oligospermia, and menstrual dysfunction. It is not known if the infertility is reversible in affected patients. Discuss the risk of effects on reproduction with female and male patients [see Use in Specific Populations (8.3)] .

5.12 Increased Toxicity Due to Third-Space Accumulation

Methotrexate can exit slowly from third‑space accumulations resulting in prolonged terminal plasma half-life and toxicity. Evacuate significant third-space accumulations prior to methotrexate administration [see Clinical Pharmacology (12.3)] .

5.13 Soft Tissue and Bone Toxicity with Radiation Therapy

Concomitant radiation therapy increases the risk of soft tissue necrosis and osteonecrosis associated with methotrexate.

5.14 Laboratory Tests

Closely monitor patients undergoing XATMEP therapy so that toxic effects are detected promptly. In general, monitoring of the following parameters is recommended: hematology at least monthly, renal function and liver function every 1 to 2 months [see Warnings and Precautions (5.1, 5.3, 5.5)] .

Increase monitoring frequency during initial dosing, dose changes, or during periods of increased risk of elevated methotrexate blood levels (e.g., dehydration).

Liver Function Tests

Transient liver function test abnormalities are observed frequently after methotrexate administration and are usually not cause for modification of methotrexate therapy. Persistent liver function test abnormalities, and/or depression of serum albumin may be indicators of serious liver toxicity and require evaluation [see Warnings and Precautions (5.5)] .

Pulmonary Function Tests

Pulmonary function tests may be useful if methotrexate-induced lung disease is suspected, especially if baseline measurements are available [see Warnings and Precautions (5.6)] .

5.15 Risk of Improper Dosing

Both the physician and pharmacist should emphasize to the patient that the recommended dose is taken one time weekly, as directed, and that mistaken daily use of the recommended dose has led to fatal toxicity [see Dosage and Administration (2.1), Overdosage (10)] .

Advise patients to measure XATMEP with an accurate milliliter measuring device. Inform patients that a household teaspoon is not an accurate measuring device and could lead to overdosage, which can result in serious adverse reactions [see Overdosage (10)] . Advise patients to ask their pharmacist to recommend an appropriate measuring device and for instructions for measuring the correct dose [see Dosage and Administration (2.1), Patient Counseling Information (17)] .

6 ADVERSE REACTIONS

The following adverse reactions are discussed in more detail in other sections of the labeling.

- Bone Marrow Suppression [see Warnings and Precautions (5.1)]
- Serious Infections [see Warnings and Precautions (5.2)]
- Renal Toxicity and Increased Toxicity with Renal Impairment [see Warnings and Precautions (5.3)]
- Gastrointestinal Toxicity [see Warnings and Precautions (5.4)]
- Hepatic Toxicity [see Warnings and Precautions (5.5)]
- Pulmonary Toxicity [see Warnings and Precautions (5.6)]
- Hypersensitivity and Dermatologic Reactions [see Warnings and Precautions (5.7)]
- Secondary Malignancies [see Warnings and Precautions (5.8)]
- Ineffective Immunization and Risks Associated with Live Vaccines [see Warnings and Precautions (5.10)]
- Infertility [see Warnings and Precautions (5.11)]
- Increased Toxicity Due to Third‑Space Accumulation [see Warnings and Precautions (5.12)]
- Soft Tissue and Bone Toxicity with Radiation Therapy [see Warnings and Precautions (5.13)]

6.1 Clinical Trials Experience

Because clinical trials are conducted under widely varying conditions, adverse reaction rates observed in the clinical trials of a drug cannot be directly compared to rates in the clinical trials of another drug, and may not reflect the rates observed in practice.

The most frequently reported adverse reactions include ulcerative stomatitis, leukopenia, nausea, and abdominal distress. Other frequently reported adverse reactions are malaise, fatigue, chills, fever, dizziness, and decreased resistance to infection. Folate deficiency states may increase methotrexate toxicity.

Polyarticular Juvenile Idiopathic Arthritis

The approximate incidences of adverse reactions reported in pediatric patients with JIA treated with oral, weekly doses of methotrexate (5 to 20 mg/m^2/week or 0.1 to 0.65 mg/kg/week) were as follows (virtually all patients were receiving concomitant nonsteroidal anti-inflammatory drugs, and some also were taking low doses of corticosteroids): elevated liver function tests, 14%; gastrointestinal reactions (e.g., nausea, vomiting, diarrhea), 11%; stomatitis, 2%; leukopenia, 2%; headache, 1.2%; alopecia, 0.5%; dizziness, 0.2%; and rash, 0.2%. Although there is experience with dosing up to 30 mg/m^2/week in JIA, the published data for doses above 20 mg/m^2/week are too limited to provide reliable estimates of adverse reaction rates.

6.2 Postmarketing Experience

Additional adverse reactions which have been identified during postmarketing use of methotrexate are listed below by organ system.

Blood and Lymphatic System Disorders:Suppressed hematopoiesis causing anemia, aplastic anemia, pancytopenia, leukopenia, neutropenia, thrombocytopenia, lymphadenopathy, lymphoproliferative disorders (including reversible), hypogammaglobulinemia

Cardiovascular:Thromboembolic events (including arterial thrombosis, cerebral thrombosis, deep vein thrombosis, retinal vein thrombosis, thrombophlebitis, and pulmonary embolus), pericarditis, pericardial effusion, hypotension

Eye Disorders:Optic neuropathy, transient blindness, blurred vision, ocular irritation, conjunctivitis, xerophthalmia

Gastrointestinal Disorders:Gingivitis, pharyngitis, stomatitis, anorexia, nausea, vomiting, diarrhea, hematemesis, melena, gastrointestinal ulceration and bleeding, enteritis, pancreatitis

Hepatobiliary Disorders:Hepatotoxicity, acute hepatitis, chronic fibrosis and cirrhosis, decreased serum albumin, liver enzyme elevations

Immune System Disorders:Vasculitis, lymphomas, and anaphylactoid reactions

Infections:Fatal opportunistic infections (most commonly Pneumocystis jirovecipneumonia). There have also been reports of other infections, pneumonia, sepsis, nocardiosis, histoplasmosis, cryptococcosis, Herpes zoster, Herpes simplexhepatitis, and disseminated Herpes simplex

Metabolism:Hyperglycemia and tumor lysis syndrome

Musculoskeletal System:Stress fracture, soft tissue necrosis, osteonecrosis, arthralgia, myalgia, osteoporosis

Nervous System Disorders:Headaches, drowsiness, blurred vision, transient blindness, speech impairment (including dysarthria and aphasia), hemiparesis, paresis and convulsions have also occurred following administration of methotrexate.

Following low doses, there have been reports of transient subtle cognitive dysfunction, mood alteration, unusual cranial sensations, leukoencephalopathy, or encephalopathy.

Renal Disorders:Azotemia, hematuria, proteinuria, cystitis

Reproductive Disorders:Defective oogenesis or spermatogenesis, menstrual dysfunction, loss of libido, impotence, vaginal discharge, gynecomastia

Respiratory Disorders:Pulmonary fibrosis, respiratory failure, chronic interstitial obstructive pulmonary disease, pleuritic pain and thickening alveolitis

Skin Disorders:Erythematous rashes, pruritus, urticaria, photosensitivity, pigmentary changes, alopecia, ecchymosis, telangiectasia, acne, furunculosis, erythema multiforme, toxic epidermal necrolysis, Stevens-Johnson syndrome, skin necrosis, skin ulceration, accelerated nodulosis, and exfoliative dermatitis.

7 DRUG INTERACTIONS

7.1 Effect of Other Drugs on XATMEP

Oral Antibiotics

Penicillins may reduce the renal clearance of methotrexate; increased serum concentrations of methotrexate with concomitant hematologic and gastrointestinal toxicity have been observed with methotrexate. Monitor patients accordingly [see Warnings and Precautions (5.1, 5.4)] .

Trimethoprim/sulfamethoxazole has been reported to increase bone marrow suppression in patients receiving methotrexate. Monitor patients accordingly [see Warnings and Precautions (5.1)] .

Hepatotoxins

The potential for increased hepatotoxicity when methotrexate is administered with other hepatotoxic agents has not been evaluated; however, hepatotoxicity has been reported in such cases. Monitor patients receiving XATMEP with other potential hepatotoxins (e.g., azathioprine, retinoids, and sulfasalazine) for possible signs of hepatotoxicity.

Probenecid

Probenecid may reduce renal elimination of methotrexate. Consider alternative drugs.

Nitrous Oxide

The use of nitrous oxide anesthesia potentiates the effect of methotrexate on folate-dependent metabolic pathways, resulting in the potential for increase toxicity. Avoid the simultaneous use of nitrous oxide and methotrexate.

Nonsteroidal Anti-Inflammatory Drugs (NSAIDs), Aspirin, and Steroids

Concomitant administration of some NSAIDs with high dose methotrexate therapy has been reported to elevate and prolong serum methotrexate levels, resulting in deaths from severe hematologic and gastrointestinal toxicity.

Caution should be used when NSAIDs and salicylates are administered concomitantly with lower doses of methotrexate, including XATMEP. These drugs have been reported to reduce the tubular secretion of methotrexate in an animal model and may enhance its toxicity.

Despite the potential interactions, studies of methotrexate in patients with rheumatoid arthritis, including patients with polyarticular juvenile idiopathic arthritis (pJIA), have usually included concurrent use of constant dosage regimens of NSAIDs, without apparent problems. It should be appreciated, however, that the doses used in pJIA (10 mg/m^2/week as starting dose) are somewhat lower than those used in acute lymphoblastic leukemia and that larger doses could lead to unexpected toxicity. Aspirin, NSAIDs, and/or low dose steroids may be continued, although the possibility of increased toxicity with concomitant use of NSAIDs including salicylates has not been fully explored. Steroids may be reduced gradually in patients who respond to methotrexate.

7.2 Effect of XATMEP on Other Drugs

Theophylline

Methotrexate may decrease the clearance of theophylline. Monitor theophylline levels when coadministered with XATMEP.

8 USE IN SPECIFIC POPULATIONS

8.1 Pregnancy

Risk Summary

Based on published reports and methotrexate’s mechanism of action, methotrexate is a teratogen that can cause embryo-fetal toxicity and fetal death when administered to a pregnant woman [see Dataand Clinical Pharmacology (12.1)] . In pregnant women with non-malignant disease, XATMEP is contraindicated. Consider the benefits and risks of XATMEP and risks to the fetus when prescribing XATMEP to a pregnant patient with a neoplastic disease. There are no animal data that meet current standards for nonclinical developmental toxicity studies.

The estimated background risk of major birth defects and miscarriage for the indicated populations are unknown. In the U.S. general population, the estimated background risk of major birth defects and miscarriage in clinically recognized pregnancies is 2-4% and 15-20%, respectively.

Data

Human Data

Published data from cases, literature reviews, and observational studies report that methotrexate exposure during pregnancy is associated with an increased risk of embryo-fetal toxicity and fetal death. Methotrexate exposure during the first trimester of pregnancy is associated with an increased incidence of spontaneous abortions and multiple adverse developmental outcomes, including skull anomalies, facial dysmorphism, central nervous system abnormalities, limb abnormalities, and sometimes cardiac anomalies and intellectual impairment. Adverse outcomes associated with exposure during second and third trimesters of pregnancy include intrauterine growth restriction and functional abnormalities. Because methotrexate is widely distributed and persists in the body for a prolonged period, there is a potential risk to the fetus from preconception methotrexate exposure.

A prospective multicenter study by U.S. and European teratology information services evaluated pregnancy outcomes in women taking methotrexate less than or equal to 30 mg/week after conception. The rate of spontaneous abortion/miscarriage in pregnant women exposed to methotrexate was 42.5% (95% confidence interval [95% CI] 29.2-58.7), which was higher than in unexposed autoimmune disease comparators (22.5%, 95% CI 16.8-29.7) and unexposed nonautoimmune disease comparators (17.3%, 95% CI 13-22.8). Of the live births, the rate of major birth defects in pregnant women exposed to methotrexate after conception was higher than in autoimmune disease comparators (adjusted odds ratio (OR) 1.8 [95% CI 0.6-5.7]) and nonautoimmune disease comparators (adjusted OR 3.1 [95% CI 1.03-9.5]). Major birth defects associated with pregnancies exposed to methotrexate after conception were not always consistent with methotrexate-associated adverse developmental outcomes.

8.2 Lactation

Risk Summary

Limited published literature report the presence of methotrexate in human milk in low amounts. The highest breast milk to plasma concentration ratio demonstrated was 0.08:1. No information is available on the effects of methotrexate on a breastfed infant or on milk production. Because of the potential for serious adverse reactions, including myelosuppression, from methotrexate in breastfed infants, advise women not to breastfeed during XATMEP therapy.

8.3 Females and Males of Reproductive Potential

Pregnancy Testing

Test for pregnancy prior to initiating therapy with XATMEP.

Contraception

Females

XATMEP can cause fetal harm when administered to a pregnant woman [see Use in Specific Populations (8.1)] .

Advise females of reproductive potential to use effective contraception during and for 6 months after the final methotrexate dose.

Males

Methotrexate can cause chromosomal damage to sperm cells. Advise males with female partners of reproductive potential to use effective contraception during and for at least 3 months after the final methotrexate dose.

Infertility

Females

Based on published reports of female infertility after therapy with methotrexate, advise females of reproductive potential that XATMEP can cause impairment of fertility and menstrual dysfunction during and after cessation of therapy. It is not known if the infertility may be reversed in all affected females.

Males

Based on published reports of male infertility after therapy with methotrexate, advise males of reproductive potential that XATMEP can cause oligospermia or infertility during and after cessation of therapy. It is not known if the infertility may be reversed in all affected males.

8.4 Pediatric Use

Safety and effectiveness of XATMEP in pediatric patients have been established for the treatment of pediatric patients with acute lymphoblastic leukemia (ALL) as part of a multi-phase, combination chemotherapy maintenance regimen and for the management of pediatric patients with active polyarticular juvenile idiopathic arthritis (pJIA) [see Clinical Studies (14)] .

8.6 Renal Impairment

Methotrexate elimination is reduced in patients with impaired renal function. Monitor patients with renal impairment for an extended period of time. Consider a dose reduction or, in some cases, discontinue XATMEP administration [see Warnings and Precautions (5.3)] .

8.7 Hepatic Impairment

The effect of hepatic impairment on methotrexate pharmacokinetics has not been studied. Patients with hepatic impairment may be more susceptible to hepatotoxicity [see Warnings and Precautions (5.5)] . Consider dose adjustments or alternative treatments in patients with baseline hepatic impairment.

10 OVERDOSAGE

Manifestations

Fatal overdosage has occurred with methotrexate. Manifestations of overdosage include adverse reactions reported at pharmacologic doses, particularly hematologic and gastrointestinal reactions (e.g., leukopenia, thrombocytopenia, anemia, pancytopenia, bone marrow suppression, mucositis, stomatitis, oral ulceration, nausea, vomiting, gastrointestinal ulceration, or gastrointestinal bleeding). In some cases, no symptoms were reported.

Management

Leucovorin and levoleucovorin are indicated to diminish the toxicity and counteract the effect of inadvertently administered overdosages of methotrexate. Administer leucovorin or levoleucovorin as soon as possible after overdosage (refer to the leucovorin or levoleucovorin Prescribing Information). Monitor serum methotrexate concentrations closely to guide leucovorin or levoleucovorin therapy. Monitor serum creatinine concentrations closely because high serum methotrexate concentrations may cause renal damage leading to acute renal failure.

Glucarpidase is indicated for the treatment of toxic methotrexate concentrations in patients with delayed methotrexate clearance due to impaired renal function (refer to the glucarpidase Prescribing Information). If glucarpidase is used, do not administer leucovorin within 2 hours before or after a dose of glucarpidase because leucovorin is a substrate for glucarpidase.

In cases of massive overdosage, hydration and urinary alkalinization may be necessary to prevent the precipitation of methotrexate and/or its metabolites in the renal tubules. Neither hemodialysis nor peritoneal dialysis has been shown to improve methotrexate elimination. However, effective clearance of methotrexate has been reported with acute, intermittent hemodialysis using a high-flux dialyzer.

11 DESCRIPTION

XATMEP contains methotrexate, a folate analog metabolic inhibitor.

Chemically methotrexate is N-[4-[[(2,4-diamino-6-pteridinyl)methyl]methylamino]-benzoyl]-L-glutamic acid. The structural formula is:

XATMEP is a clear yellow to orange oral solution that contains 2.5 mg of methotrexate per milliliter (equivalent to 2.74 mg of methotrexate sodium/mL). Inactive ingredients include purified water, sodium citrate, citric acid, methylparaben sodium, propylparaben sodium, and sucralose. It may also contain sodium hydroxide or hydrochloric acid for pH adjustment.

12 CLINICAL PHARMACOLOGY

12.1 Mechanism of Action

Methotrexate inhibits dihydrofolic acid reductase. Dihydrofolates must be reduced to tetrahydrofolates by this enzyme before they can be utilized as carriers of one-carbon groups in the synthesis of purine nucleotides and thymidylate. Therefore, methotrexate interferes with DNA synthesis, repair, and cellular replication. Actively proliferating tissues such as malignant cells, bone marrow, fetal cells, buccal and intestinal mucosa, and cells of the urinary bladder are in general more sensitive to this effect of methotrexate.

The mechanism of action in pJIA is unknown; it may affect immune function.

12.2 Pharmacodynamics

Two reports describe in vitromethotrexate inhibition of DNA precursor uptake by stimulated mono-nuclear cells, and another describes in animal polyarthritis partial correction by methotrexate of spleen cell hyporesponsiveness and suppressed IL 2 production. Other laboratories, however, have been unable to demonstrate similar effects.

12.3 Pharmacokinetics

Absorption

In pediatric patients with ALL, oral absorption of methotrexate appears to be dose dependent; the absorption of doses greater than 40 mg/m^2is significantly less than that of lower doses. The extent of oral absorption ranges from 23% to 95%, and the time to peak concentration (Tmax) ranges from 0.7 hours to 4 hours after an oral dose of 15 mg/m^2.

In pediatric patients with pJIA, mean serum concentrations were 0.59 micromolar (range, 0.03 to 1.40) at 1 hour, 0.44 micromolar (range, 0.01 to 1.00) at 2 hours, and 0.29 micromolar (range 0.06 to 0.58) at 3 hours following oral administration of methotrexate at a dose of 6.4 mg/m^2/week to 11.2 mg/m^2/week.

Effect of Food

The administration of XATMEP with food did not affect the area under the curve (AUC), but decreased the maximal concentrations (Cmax) by 50% and delayed the absorption.

Distribution

After intravenous administration, the initial volume of distribution is approximately 0.18 L/kg (18% of body weight) and steady-state volume of distribution is approximately 0.4 to 0.8 L/kg (40% to 80% of body weight).

Methotrexate competes with reduced folates for active transport across cell membranes by means of a single carrier-mediated active transport process. At serum concentrations greater than 100 micromolar, passive diffusion becomes a major pathway by which effective intracellular concentrations can be achieved.

Methotrexate in serum is approximately 50% protein bound.

Methotrexate does not penetrate the blood-cerebrospinal fluid barrier in therapeutic amounts when given orally.

Elimination

In adults, the half-life of methotrexate following administration of low dose methotrexate (less than 30 mg/m^2) ranges from 3 hours to 10 hours.

In pediatric patients receiving methotrexate for ALL (6.3 mg/m^2 to 30 mg/m^2), the terminal half-life has been reported to range from 0.7 hours to 5.8 hours.

In pediatric patients receiving methotrexate for JIA (3.75 mg/m^2to 26.2 mg/m^2), the terminal half-life has been reported to range from 0.9 hours to 2.3 hours.

Metabolism

Methotrexate undergoes hepatic and intracellular metabolism to polyglutamated forms which can be converted back to methotrexate by hydrolase enzymes. These polyglutamates act as inhibitors of dihydrofolate reductase and thymidylate synthetase. Small amounts of methotrexate polyglutamates may remain in tissues for extended periods. The retention and prolonged drug action of these active metabolites vary among different cells, tissues and tumors. A small amount of metabolism to 7‑hydroxymethotrexate may occur at doses commonly prescribed. The aqueous solubility of 7‑hydroxymethotrexate is 3- to 5-fold lower than the parent compound. Methotrexate is partially metabolized by intestinal flora after oral administration.

Excretion

Renal excretion is the primary route of elimination and is dependent upon dosage and route of administration. With IV administration, 80% to 90% of the administered dose is excreted unchanged in the urine within 24 hours. There is limited biliary excretion amounting to 10% or less of the administered dose. Enterohepatic recirculation of methotrexate has been proposed.

Renal excretion occurs by glomerular filtration and active tubular secretion. Nonlinear elimination due to saturation of renal tubular reabsorption has been observed in patients at doses between 7.5 mg and 30 mg. Impaired renal function, as well as concurrent use of drugs such as weak organic acids that also undergo tubular secretion, can markedly increase methotrexate serum levels.

Methotrexate clearance decreases at higher doses. Delayed drug clearance has been identified as one of the major factors responsible for methotrexate toxicity. When a patient has delayed drug elimination due to compromised renal function, a third-space effusion, or other causes, methotrexate serum concentrations may remain elevated for prolonged periods.

13 NONCLINICAL TOXICOLOGY

13.1 Carcinogenesis, Mutagenesis, Impairment of Fertility

Methotrexate has been evaluated in a number of animal studies for carcinogenic potential with inconclusive results. Although there is evidence that methotrexate causes chromosomal damage to animal somatic cells and human bone marrow cells, the clinical significance remains uncertain.

14 CLINICAL STUDIES

Polyarticular Juvenile Idiopathic Arthritis

Clinical trials in patients with polyarticular juvenile idiopathic arthritis were performed using other formulations of methotrexate.

In a 6-month, double-blind, placebo-controlled trial of 127 pediatric patients with juvenile idiopathic arthritis (JIA) (mean age, 10.1 years; age range 2.5 to 18 years, mean duration of disease, 5.1 years) on background non-steroidal anti-inflammatory drugs (NSAIDs) and/or prednisone, methotrexate given one time weekly at an oral dose of 10 mg/m^2provided significant clinical improvement compared to placebo as measured by either the physician’s global assessment, or by a patient composite (25% reduction in the articular-severity score plus improvement in parent and physician global assessments of disease activity). Over two-thirds of the patients in this trial had polyarticular-course JIA, and the numerically greatest response was seen in this subgroup treated with 10 mg/m^2/week methotrexate. The overwhelming majority of the remaining patients had systemic-course JIA. All patients were unresponsive to NSAIDs; approximately one-third were using low dose corticosteroids. Weekly methotrexate at a dose of 5 mg/m^2was not significantly more effective than placebo in this trial.

15 REFERENCES

1. “Hazardous Drugs” OSHA. http://www.osha.gov/SLTC/hazardousdrugs/index.html

16 HOW SUPPLIED/STORAGE AND HANDLING

XATMEP is a clear yellow to orange oral solution that contains 2.5 mg of methotrexate per milliliter (equivalent to 2.74 mg of methotrexate sodium/mL). It is packaged in a high-density polyethylene (HDPE) bottle with a child-resistant cap and tamper-evident seal.

XATMEP is available in bottles of 60 mL (NDC 52652-2001-6) and 120 mL (NDC 52652-2001-1).

Store XATMEP refrigerated (2°C to 8°C/36°F to 46°F) tightly closed in the original container prior to dispensing.

Once dispensed, patients may store XATMEP either refrigerated (2°C to 8°C/36°F to 46°F) or at room temperature (20°C to 25°C/68°F to 77°F) with excursions permitted to 15°C to 30°C/59°F to 86°F [see USP Controlled Room Temperature]. If stored at room temperature, discard after 60 days. Avoid freezing and excessive heat.

17 PATIENT COUNSELING INFORMATION

Importance of Proper Dosing and Administration

Advise patients that the recommended dose should be taken one timeweekly, as directed, and that mistaken daily use of the recommended dose has led to fatal toxicity [see Dosage and Administration (2.1), Warnings and Precautions (5.15)].

Advise patients and caregivers to measure XATMEP with an accurate milliliter measuring device. A household teaspoon is not an accurate measuring device. Advise patients and caregivers to ask their pharmacist to recommend an appropriate measuring device and for instructions for measuring the correct dose.

Bone Marrow Suppression and Serious Infections

Advise patients to contact their healthcare provider for new onset fever, symptoms of infection, easy bruising or persistent bleeding [see Warnings and Precautions (5.1, 5.2)] .

Renal Toxicity

Advise patients that methotrexate can cause renal toxicity [see Warnings and Precautions (5.3)] .

Gastrointestinal Toxicity

Advise patients to contact their healthcare provider if they develop diarrhea, vomiting, or stomatitis [see Warnings and Precautions (5.4)] .

Hepatic Toxicity

Advise patients concerning the risk of hepatic toxicity and avoidance of alcohol during methotrexate treatment [see Warnings and Precautions (5.5)] .

Pulmonary Toxicity

Advise patients to contact their healthcare provider for symptoms of cough, fever, and dyspnea [see Warnings and Precautions (5.6)] .

Hypersensitivity Reactions

Advise patients concerning the risk for severe hypersensitivity reactions due to XATMEP treatment. These can be fatal and may include severe dermatologic reactions such as toxic epidermal necrolysis, Stevens-Johnson syndrome, exfoliative dermatitis, and erythema multiforme. Advise patients to contact their healthcare provider for signs of a new or worsening rash [see Warnings and Precautions (5.7)] .

Secondary Malignancies

Advise patients that there is a risk of secondary malignancies during or following treatment with XATMEP [see Warnings and Precautions (5.8)] .

Embryo-Fetal Toxicity

Advise females of reproductive potential of the potential risk to a fetus and to inform their healthcare provider of a known or suspected pregnancy [see Boxed Warning, Contraindications (4), Warnings and Precautions (5.9), Use in Specific Populations (8.1)] .

Advise females of reproductive potential to use effective contraception during XATMEP therapy and for 6 months after the final dose [see Use in Specific Populations (8.3)] .

Advise males of reproductive potential to use effective contraception during XATMEP therapy and for 3 months after the final dose [see Use in Specific Populations (8.3)] .

Ineffective Immunization and Risks Associated with Live Vaccines

Advise patients to avoid receiving vaccines during treatment with XATMEP because they may not be effective and live virus vaccines may cause infection [see Warnings and Precautions (5.10)] .

Infertility

Advise patients of reproductive potential that XATMEP may cause impairment of fertility, oligospermia, and menstrual dysfunction [see Warnings and Precautions (5.11), Use in Specific Populations (8.3)] .

Lactation

Advise females not to breastfeed during therapy with XATMEP [see Use in Specific Populations (8.2)] .

Proper Storage and Disposal

Advise patients to store XATMEP either refrigerated (2°C to 8°C/36°F to 46°F) or at room temperature (20°C to 25°C/68°F to 77°F) with excursions permitted to 15°C to 30°C/59°F to 86°F. If stored at room temperature, discard after 60 days. Inform patients and caregivers of the need for proper storage and disposal of dispensing bottles and dosing devices [see References (15)] .

Manufactured for:

Azurity Pharmaceuticals, Inc.
Wilmington, MA 01887 USA

U.S. Patent: 9,259,427; 9,855,215

This product’s label may have been updated. For current full prescribing information, please visit www.xatmep.com

PI100072.03 Rev. 9/2020

PRINCIPAL DISPLAY PANEL - 120 mL Bottle Label

NDC 52652-2001-1

Xatmep®
(methotrexate)

Oral Solution
2.5 mg/mL

For Oral Use Only

CAUTION: Cytotoxic agent

120 mL

azurity
pharmaceuticals

Rx Only

Each 1 mL contains 2.5 mg
methotrexate (equivalent to
2.74 mg methotrexate sodium).

Usual Dose:
See prescribing information.

KEEP THIS AND ALL MEDICATIONS
OUT OF THE REACH OF CHILDREN

Store refrigerated
2° - 8°C (36° - 46°F)
Patients may store Xatmep
either refrigerated or at
room temperature
(20° - 25°C/68° - 77°F).

If stored at room temperature,
discard after 60 days.

Discard on

_____/_____/_____

Manufactured for:
Azurity Pharmaceuticals, Inc.
Wilmington, MA 01887 USA

Lot:
Exp: